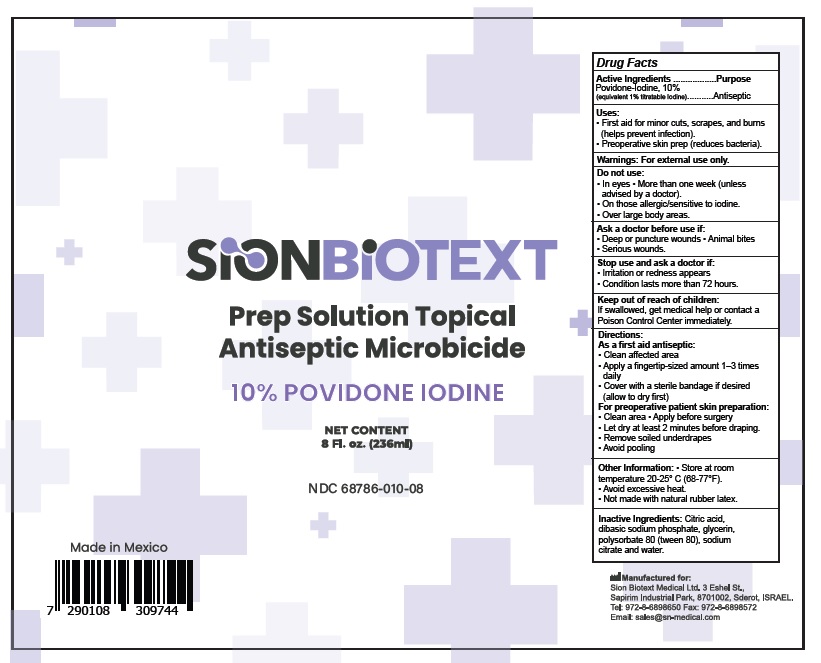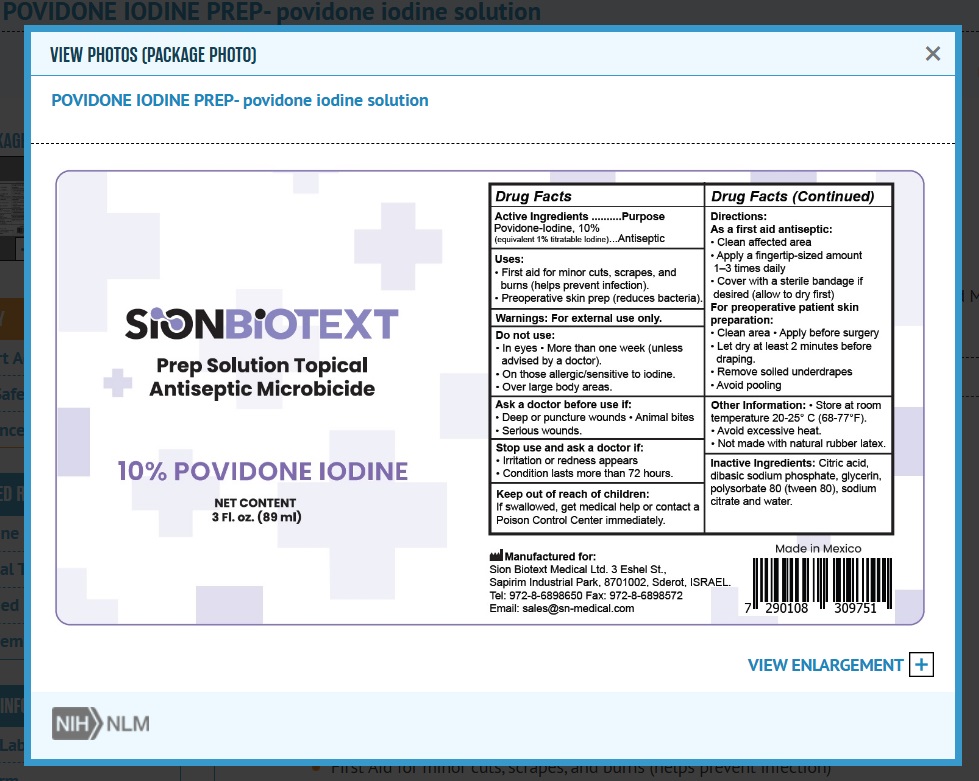 DRUG LABEL: Povidone Iodine Prep
NDC: 68786-010 | Form: SOLUTION
Manufacturer: Sion Biotext Medical Ltd
Category: otc | Type: HUMAN OTC DRUG LABEL
Date: 20250611

ACTIVE INGREDIENTS: POVIDONE-IODINE 10 g/100 mL
INACTIVE INGREDIENTS: CITRIC ACID MONOHYDRATE; SODIUM PHOSPHATE, DIBASIC; GLYCERIN; WATER; SODIUM CITRATE; POLYSORBATE 80

Drug Facts

Active ingredient

Povidone-Iodine 10% (equivalent to 1% titrable Iodine)

Purpose

Antiseptic

Uses

- First Aid for minor cuts, scrapes, and burns (helps prevent infection)
- Preoperative skin prep (reduces bacteria)

Warning

For external use only.

Do Not Use:

- In eyes
- More than week (unless advised by a doctor)
- On those allergic/senstiive to iodine
- Over large body areas

Ask a doctor before use if:

- Deep or puncure wounds.
- Animal Bites
- Serious wounds

Stop use and ask a doctor if:

- Irritation or redness appears
- Condition lasts more than 72 hours

Keep out of reach of children

If swallowed, get medical help or contact a Poison Control Center immediately

Directions

As a first aid antiseptic:

- Clean affected area
- Apply a fingertip-sized amount 1-3 tmes daily
- Cover with a sterile bandage if desired (allow to dry first)

For preoperative patient skin preparation:

- Clean area
- Apply before surgery
- Let dry at least 2 minutes before draping
- Remove soiled underdrapes
- Avoid pooling

Other Information

- Store at room temperature 20-25° C (68-77°F)
- Avoid excessive heat
- Not made with natural rubber latex

Inactive Ingredients

Citric acid, dibasic sodium phosphate, glycerin, polysorbate 80 (tween 80), sodium citrate, water.

Principal Display Panel

NDC 68786-010-89

SIONBIOTEXT

Prep Solution Topical Antiseptic Microbicide

10% POVIDONE IODINE

NET CONTENT

3 fl.oz. (89 ml)

NDC 68786-010-08

SIONBIOTEXT

Prep Solution Topical Antiseptic Microbicide

10% POVIDONE IODINE

NET CONTENT

8 Fl.oz. (236 ml)